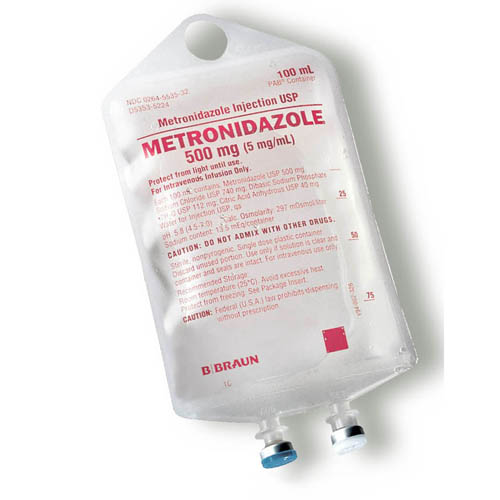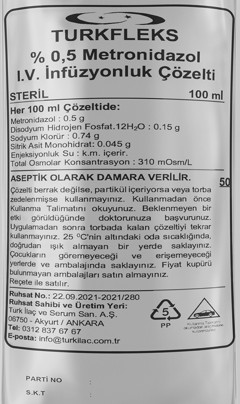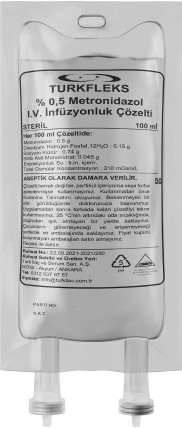 DRUG LABEL: Turkfleks %0.5 Metronidazole Infusion Solution
NDC: 85160-100 | Form: INJECTION, SOLUTION
Manufacturer: TURK ILAC VE SERUM SANAYI ANONIM SIRKETI
Category: prescription | Type: HUMAN PRESCRIPTION DRUG LABEL
Date: 20250330

ACTIVE INGREDIENTS: METRONIDAZOLE 500 mg/100 mL

DESCRIPTION

NAME OF THE HUMAN MEDICAL PRODUCT

TURKFLEKS 0.5% METRONIDAZOL IV solution for infusion Sterile

QUALITATIVE AND QUANTITATIVE COMPOSITION

Active ingredient:

Each 100 ml of solution contains 500 mg of metronidazole.

Excipient(s):

Disodium hydrogen phosphate dodecahydrate….............. 150 mg

Sodium chloride…...................................................... 740 mg

Excipients:

Disodium hydrogen phosphate dodecahydrate

Sodium chloride

Citric acid monohydrate

Water for injection

INTENDED USE OF THE DEVICE

Medical and surgical infections caused by anaerobic bacteria sensitive to metronidazole in the treatment of infections,
For prophylactic purposes in surgical procedures with a risk of anaerobic infection development,
It is indicated in severe intestinal and hepatic amebiasis.

INDICATIONS AND USAGE

Medical and surgical infections caused by anaerobic bacteria sensitive to metronidazole in the treatment of infections,
For prophylactic purposes in surgical procedures with a risk of anaerobic infection development,
It is indicated in severe intestinal and hepatic amebiasis.

CONTRAINDICATIONS

Contraindicated in those with hypersensitivity to imidazole derivatives or excipients

CLINICAL PHARMACOLOGY

Solution for infusion.

Colourless, for intravenous infusion.

Clear and particle-free sterile isotonic solution.

Posology and method of administration

Dosage/frequency and duration of application:

Treatment of medical and surgical infections caused by susceptible anaerobic bacteria: Adults: 1 – 1.5 g/day in 2 or 3 equal doses intravenously.

Children: Intravenous single dose of 20-30 mg/kg/day or 7.5 mg/kg every 8 hours for children aged 8 weeks to 12 years. Depending on the severity of the infection, the daily dose may be increased to 40 mg/kg. The duration of treatment is usually 7 days.

Children younger than 8 weeks: 15 mg/kg once daily or 7.5 mg/kg every 12 hours. Metronidazole accumulation may occur in neonates younger than 40 weeks gestational age during the first week after birth. Therefore, serum metronidazole concentrations may need to be monitored during the first few days of treatment. Once the patient is able to take the medication orally, treatment should be continued with the same oral dose.

Prophylactic treatment in surgical procedures with a risk of anaerobic infection:

In this indication, metronidazole should be combined with a drug effective against enterobacteriaceae.

Adults: 500 mg by intravenous infusion (administered over 30 to 60 minutes) immediately before surgery and at 8 and 16 hours after surgery.

Children under 12 years of age: 20–30 mg/kg as a single dose, 1–2 hours before surgery.

In neonates with a gestational age of less than 40 weeks: 10 mg/kg as a single dose before surgery.

Severe intestinal amebiasis:

Adults: 1.5 g/day (e.g. 3 intravenous infusions of 500 mg per day)

Children over 10 years: 400-800 mg 3 times daily for 5-10 days.

Children 7-10 years old: 200-400 mg 3 times daily for 5-10 days.

Children 3-7 years: 100-200 mg 4 times daily for 5-10 days

Children 1-3 years: 100-200 mg 3 times daily for 5-10 days

Alternatively, the dose can be adjusted according to body weight. 35-50 mg/kg daily in 3 divided doses for 5-10 days. The daily dose should not exceed 2400 mg.

In hepatic amebiasis, abscess drainage should be applied together with metronidazole treatment during the abscess period.

Method of

application: 5 ml per minute is administered as an infusion.

Additional information regarding special populations:

Kidney/Liver failure:

In severe hepatic insufficiency, the dose and frequency of administration should be adjusted according to the degree of insufficiency and serum levels of metronidazole. For renal insufficiency , see section 4.4.

Pediatric population:

Given above.

Geriatric population:

Caution is recommended in the elderly. Caution should be exercised especially at high doses.

WARNINGS AND PRECAUTIONS

Long-term use of TURKFLEKS 0.5% METRONIDAZOL in treatment should be carefully evaluated (see section 5.3). In case of longer-than-planned use, regular blood tests should be performed, and leukocytes should be monitored in particular and attention should be paid to the development of neuropathy.

Due to the risk of exacerbation of neurological symptoms, active or chronic peripheral or Should be used with caution in patients with central neurological disorders.
Patients should be warned not to drink alcohol during treatment and for at least two days after stopping treatment, as it may cause a disulfiram-like reaction.
It should be used with caution in patients with blood dyscrasia findings or history. Leukocyte count should be performed before and after treatment. In cases with blood dyscrasia or high dose and/or long-term treatment, the decision on whether to continue treatment should be made according to the severity of the infection. Adverse reactions should be monitored in treatments longer than 10 days.

Metronidazole should be used with caution in cases of hepatic encephalopathy. The daily dose should be reduced to one third and used as a single dose.
It may darken the urine color due to its metabolites; patients should be informed about this. • Oral, vaginal or intestinal candidiasis

after intravenous metronidazole use

may develop.

It has no direct activity against aerobic and facultative anaerobic bacteria.

After Trichomonas vaginalis is eliminated, a gonococcal infection does not remain

There is a possibility.

In case of renal failure, the elimination half-life of metronidazole does not change.

Therefore, there is no need to reduce the dose of metronidazole. However, metronidazole metabolites remain in these patients. The clinical significance of this is unknown.

In patients receiving hemodialysis, metronidazole and its metabolites are effectively removed within an 8- hour dialysis period. Therefore, metronidazole should be re-administered immediately after hemodialysis.

There is no routine dosage adjustment

necessary in patients with renal failure receiving intermittent peritoneal dialysis (IPD) or continuous ambulatory peritoneal dialysis (CAPD).

If ataxia, vertigo, hallucinations or confusion are observed, treatment should be discontinued.
Metronidazole potentiates the effect of vecuronium, which is used to create non-depolarizing neuromuscular blockade.
Although metronidazole has been found to be carcinogenic in a certain mouse species, this effect has not been demonstrated in rats and hamsters. The preparation has no such effect in humans.

Due to insufficient evidence of mutagenicity risk in humans

Use of TURKFLEKS 0.5% METRONIDAZOL for a longer period than usual should be carefully evaluated.

This medicinal product contains 13 mmol sodium per 100 ml. Patients on a low sodium and low salt diet should be careful. It should also be administered with caution to those prone to oedema.

Should be stored at room temperature below 25 °C.

OTHER SAFETY INFORMATION

1.1. Interactions with other medical products and other forms of interaction

Disulfiram: Psychotic reactions have been reported in patients using disulfiram together with metronidazole.
Alcohol: In order to avoid a disulfiram-type reaction (redness in the face and neck area, vomiting, tachycardia), alcoholic beverages or medications containing alcohol should not be consumed during treatment and for at least 2 days after the end of treatment.
Warfarin: Since metronidazole reduces the destruction of oral anticoagulants in the liver, the effect of these preparations and the risk of hemorrhage may increase when used together. Therefore, in combined use, prothrombin levels should be checked frequently and the oral anticoagulant dose to be applied should be adjusted.
Lithium: Plasma levels of lithium may increase when used with metronidazole.

Therefore, plasma concentrations of lithium, creatinine and electrolytes should be monitored in patients receiving metronidazole while on lithium therapy.

Cyclosporine: Increased serum levels of cyclosporine may occur.

If co-administration with metronidazole is necessary, serum cyclosporine and creatinine levels should be closely monitored.

Phenytoin-phenobarbital: Elimination of metronidazole may be increased and a decrease in serum levels may be observed.
5-fluoro-uracil: When used with metronidazole, the excretion of 5-fluoro-uracil decreases and its toxic effects increase accordingly.
Busulfan: Since metronidazole will increase the plasma busulfan amount, serious busulfan

may cause toxicity.

Interference with laboratory tests: Metronidazole may cause changes in AST (SGOT), ALT (SGPT), LDH, triglycerides, or glucose measurements when measured using the ultraviolet absorbance method.

PEDIATRIC USE

It can be used in children from 8 weeks of age. For necessary dosage adjustment in pediatric patients:

Treatment of medical and surgical infections caused by susceptible anaerobic bacteria: Adults: 1 – 1.5 g/day in 2 or 3 equal doses intravenously.

Children: Intravenous single dose of 20-30 mg/kg/day or 7.5 mg/kg every 8 hours for children aged 8 weeks to 12 years. Depending on the severity of the infection, the daily dose may be increased to 40 mg/kg. The duration of treatment is usually 7 days.

Children younger than 8 weeks: 15 mg/kg once daily or 7.5 mg/kg every 12 hours. Metronidazole accumulation may occur in neonates younger than 40 weeks gestational age during the first week after birth. Therefore, serum metronidazole concentrations may need to be monitored during the first few days of treatment. Once the patient is able to take the medication orally, treatment should be continued with the same oral dose.

Prophylactic treatment in surgical procedures with a risk of anaerobic infection:

In this indication, metronidazole should be combined with a drug effective against enterobacteriaceae.

Adults: 500 mg by intravenous infusion (administered over 30 to 60 minutes) immediately before surgery and at 8 and 16 hours after surgery.

Children under 12 years of age: 20–30 mg/kg as a single dose, 1–2 hours before surgery.

In neonates with a gestational age of less than 40 weeks: 10 mg/kg as a single dose before surgery.

Severe intestinal amebiasis:

Adults: 1.5 g/day (e.g. 3 intravenous infusions of 500 mg per day)

Children over 10 years: 400-800 mg 3 times daily for 5-10 days.

Children 7-10 years old: 200-400 mg 3 times daily for 5-10 days.

Children 3-7 years: 100-200 mg 4 times daily for 5-10 days

Children 1-3 years: 100-200 mg 3 times daily for 5-10 days

Alternatively, the dose can be adjusted according to body weight. 35-50 mg/kg daily in 3 divided doses for 5-10 days. The daily dose should not exceed 2400 mg.

In hepatic amebiasis, abscess drainage should be applied together with metronidazole treatment during the abscess period.

PREGNANCY

General

recommendation Pregnancy category: B (2nd and 3rd trimester)

Women of childbearing potential/Birth control (Contraception)

Caution should be exercised in women of childbearing potential.

Pregnancy Period

There is insufficient information on the safety of metronidazole during pregnancy. Its use is not strictly necessary. It should not be given during pregnancy unless it is necessary. If its use is unavoidable, it is used for short periods. and a low-dose regimen is recommended.

LACTATION

Metronidazole should not be used by breastfeeding mothers as it passes into breast milk

FEMALES AND MALES OF REPRODUCTIVE POTENTIAL

Metronidazole has been shown to be mutagenic in bacteria in vitro . In vivo human cell culture studies have not provided adequate evidence of mutagenic effects

ADVERSE REACTIONS

Adverse reactions reported more frequently than placebo in clinical trials and defined as at least possibly attributable to metronidazole treatment based on the best assessment of causality from available data are listed below using

the following classification:

Very common (ÿ1/10); common (ÿ1/100 to <1/10); uncommon (ÿ1/1000 to <1/100); rare (ÿ1/10000 to <1/1000); very rare (ÿ1/10000), not known (cannot be estimated from the available data).

Blood and lymphatic system diseases

Very rare: Agranulocytosis, neutropenia, thrombocytopenia, pancytopenia. Unknown: Leukopenia

Immune system diseases

Rare: Anaphylaxis

Not known: Angioedema, urticaria, fever

Metabolism and nutritional diseases

Unknown: Anorexia

Psychiatric diseases

Very rare: Psychotic disorders including confusion and hallucinations. Unknown: Depressed mood

Nervous system diseases

Very rare: Encephalopathy (e.g., confusion, headache, hallucination, paralysis, photosensitivity, movement disorder, neck stiffness) and subacute cerebellar syndrome (e.g., ataxia, dysarthria, gait disturbance, nystagmus, and tremor), reversible on discontinuation of the drug.

Dizziness, lightheadedness, convulsions, headache.

Not known: Peripheral sensory neuropathy or transient epileptiform seizures have been reported during intensive and/or prolonged metronidazole therapy. In many cases, the neuropathy resolved after discontinuation of therapy or reduction of dosage. Aseptic meningitis.

Eye diseases

Very rare: Visual disturbances such as diplopia or myopia, mostly transient, blurred vision, decreased visual acuity, changes in colour vision.

Not known: Optic neuropathy/neuritis

Gastrointestinal diseases

Not known: Taste changes, oral mucositis, furry tongue, tongue discoloration/hairiness, gastrointestinal disorders such as nausea, vomiting, epigastric pain and diarrhoea. Cases of reversible pancreatitis.

Hepatobiliary diseases

Very rare: Increases in liver enzymes (AST, ALT, ALP), sometimes with jaundice, cholestatic hepatitis or mixed hepatitis and hepatocellular liver damage have been reported. Cases of liver failure requiring liver transplantation have been reported in patients treated with metronidazole in combination with other antibiotics.

Skin and subcutaneous tissue diseases

Very rare: Skin rash, pustular rash, pruritus, flushing

Not known: Including erythema multiforme, Stevens-Johnson syndrome, and toxic epidermal necrolysis.

Musculoskeletal disorders, connective tissue and bone diseases

Very rare: Myalgia, arthralgia

Kidney and urinary diseases

Very rare: Darkening of urine colour (due to metronidazole metabolite) General disorders and diseases related to the application area Uncommon: Fever

Reporting of suspected adverse reactions

Reporting of suspected adverse reactions after licensing is of great importance. Reporting allows continuous monitoring of the benefit/risk balance of the drug. Healthcare professionals are required to report any suspected adverse reactions to the Turkish Pharmacovigilance Center (TÜFAM) (www.titck.gov.tr ; e-mail: tufam@titck.gov.tr ; tel: 0 800 314 00 08, fax: 0 312 218 35 99).

OVERDOSAGE

Overdose symptoms include vomiting, ataxia and disorientation.

There is no specific antidote. Symptomatic and supportive treatment should be applied.

PHARMACODYNAMICS

Pharmacotherapeutic group: Antibacterials for systemic use. ATC code: J01XD01

Mechanism of action

Metronidazole is an antibiotic from the 5-nitroimidazole group. It is bactericidal, amoebicidal and trichomonocidal.

Its antimicrobial mechanism of action is not yet known. It is not ionized at physiological pH and is taken into

the cells by anaerobic microorganisms and cells. It is reduced to polar metabolites that do not have nitro groups and are not yet fully identified by electron transport proteins with low redox potential in cells. It is thought that reduced metabolites create an antimicrobial effect by inhibiting nucleic acid synthesis and damaging DNA. Metronidazole is equally effective on dividing and non-dividing cells. In vitro and in vivo studies have also shown that metronidazole has a direct anti-inflammatory effect by affecting neutrophil motility, lymphocyte formation and cellular immunity.

Antibacterial spectrum of action of metronidazole:

Anaerobic bacteria:

Metronidazole is effective against many bacteria in vitro : Bacteroides fragilis, B. bivius (Prevotella bivia), B. disiens (Prevotella disiens), B. distasoni, B. gingivalis, (Porphyromonas gingivalis), B. intermedius (Prevotella intermedia),

B. melaninogenicus (Prevotella meloninogenica), B. oralis (Prevotella). oralis), B. ovatus, B. thetaiotaomicron, B. vulgatus, B. asaccharolyticus (Porphyromonas asaccharolytica), B. ureolyticus, Fusobacterium and Veillonella.

Some species of Mobiluncus (motile, anaerobic and those with coiled rods) are inhibited by metronidazole in vitro , while other species are considered resistant.

Gram positive anaerobic cocci that are effective against the drug are Clostiridium, C. difficile, C. perfringens, Eubacterium, Peptococcus and Peptostreptococcus. Actinomyces, Lactobacillus, Propionibacterium acnes,

P. avidum and P. granulosum are known to be resistant.

Other microorganisms:

Metronidazole is effective against Campylobacter fetus in vitro . Gardnerella vaginalis (Haemophilus vaginalis) is sensitive to high doses of metronidazole. Metronidazole was found to be ineffective against fungi in in vitro studies.

Resistance

Some strains of Trichomonas vaginalis have developed resistance to metronidazole. Rarely, Bacteroides fragilis and other anaerobic bacteria may also acquire resistance after long-term use. Resistance to metronidazole may be due to poor cell penetration and/or nitroreductase activity.

PHARMACOKINETICS

General Features

Absorption:

Since it is administered by injection, all of the administered medication is transferred to the body.

Distribution:

The mean serum levels obtained as a result of intravenous infusion of a solution containing 500 mg metronidazole over 20 minutes are 18 mcg/mL. If the same dose is repeated at 8 hour intervals, the serum levels are maintained. If it is repeated at 12 hour intervals, the serum level is 13 mcg/mL. The plasma half-life is 8-10 hours. Protein binding is low (less than 10%). Its distribution is rapid and its concentration is high in the lungs, kidneys, liver, skin, bile, cerebrospinal fluid, saliva, seminal fluid and vaginal secretions.

Metronidazole crosses the placenta and breast milk.

Biotransformation:

It is metabolized in the liver and is found in high concentrations in the liver and bile. Metronidazole is metabolized in the body into two metabolites with antibacterial activity.

“Alcohol” metabolite is the primary metabolite. Bactericidal effect against anaerobic bacteria 30% of the potency of metronidazole. Elimination half-life is approximately 11 hours.
The “acid” metabolite is present in small amounts and has a bactericidal effect of 5% of metronidazole.

There is.

Elimination:

Excretion occurs mainly via the urine (40-70% of metronidazole excreted unchanged) and therefore the urine may take on a red-brown colour.

CLINICAL STUDIES

Metronidazole has been shown to be carcinogenic in mice and rats following chronic oral administration. However, similar studies in hamsters have yielded negative results.

Epidemiological studies have shown no clear increase in carcinogenic risk in humans.

No evidence was obtained. Therefore, long-term use of TURKFLEKS 0.5% METRONIDAZOL in treatment should be carefully evaluated.

Metronidazole has been shown to be mutagenic in bacteria in vitro . In vivo human cell culture studies have not provided sufficient evidence of mutagenic effects.

HOW SUPPLIED

Sterile

OTHER SAFETY INFORMATION

To determine whether the solutions to be used together will not cause any incompatibility.

Care should be taken to ensure that the mixture is clear.

TURKFLEKS 0.5% METRONIDAZOL should not be mixed with cefamendol-naftate, cefoxitin sodium, 10% dextrose, sodium lactate, penicillin G potassium.

Shelf life

24 months.

COMPONENTS

TURKFLEKS 0.5% METRONIDAZOL, 100 ml containing 0.5 g/100 ml metronidazole It is offered in polypropylene bags, in sets and unset forms.

DISPOSAL AND WASTE HANDLING

Unused products or waste materials should be disposed of in accordance with the “Medical Waste Control Regulation” and

It must be destroyed in accordance with the “Packaging and Packaging Waste Control Regulation”.

HEALTH CARE PROVIDER LETTER

March 31, 2025

Subject: Temporary importation of Turkfleks %0.5 Metronidazole IV Solution from Turk Ilac located in Ankara-TURKEY to address drug shortages per:

https://dps.fda.gov/drugshortages/activeingredient/metronidazole-injection

To prevent a shortage of large volume parenteral fluid drug products, Turk Ilac ve Serum Sanayi is coordinating with the U.S. Food and Drug Administration (FDA) to temporarily import Turkfleks %0.5 Metronidazole IV Solution 100ml from Turk Ilac ve Serum Sanayi manufacturing facility located in Ankara/TURKEY. FDA has not approved these products manufactured by Turk Ilac ve Serum Sanayi.

Effective immediately, and during this temporary period, Turk Ilac ve Serum Sanayi will offer the following imported product from Turk Ilac ve Serum Sanayi facility located in Ankara/TURKEY:

Product Name and Description | Volume | Bags per Box | NDC Code
Turkfleks %0.5 Metronidazole | 100ml | 50 | 85160-100-10

Please note the following:

- Upon receiving Submission Acceptance Turk Ilac ve Serum Sanayi will have bag labels written in both Turkish and English.
- The bag labels will contain the active pharmaceutical ingredient, concentration, volume, and NDC code in English.
- The imported products' administration port system is fully compatible with sets marketed in the United States.
- The imported products use a carton box that is taped closed. To avoid damage to the solution container, take care not to use sharp instruments to open the box.
- The imported products do not contain barcodes on the unit label. Alternative procedures should be followed to ensure that the correct drug product is being used in all systems and processes and administered to individual patients. For example, institutions should consider manually inputting the product into their systems and confirm that barcode systems do not provide incorrect information when the product is scanned.
- %0.5 Metronidazole is available only by prescription in the United States. However, the imported products do not have the statement "Rx only" on the labeling.
- USE A NEW BAG IF PARTICULATES ARE VISIBLE OR IF THE IV BAG CONTAINS A LEAK.

Additional key differences in the labeling between the FDA-approved product and the imported products are stated in the product comparison table at the end of this letter as follows:

Table 1. Key differences between FDA-approved and Turkfleks %0.5 Metronidazole

Table 2. Label images of FDA-approved and Turkfleks %0.5 Metronidazole

Reporting Adverse Events or Product Quality Issues

To report adverse events associated with these imported products, please use the contact us at info@turkilac.com.tr.

Adverse events or quality problems experienced with the use of these imported products may also be reported to the FDA's MedWatch Adverse Event Reporting program either online, by regular mail or by fax:

- Complete and submit the report Online: www.fda.gov/medwatch/report.htm
- Regular mail or Fax: Download form www.fda.gov/MedWatch/getforms.htm

or call 1-800332-1088 to request a reporting form, then complete and return to the address on the preaddressed form or submit by fax to 1-800-FDA-0178 (1-800-332-0178).

Sincerely,

Mehmet Berat Battal

Table 1: Key Differences between FDA Approved product and Turkfleks %0.9 Sodium Chloride

 | FDA- Approved Product | Turkfleks Import from Turkey
Product Name | Metronidazole Injection USP 500 mg (5 mg/mL) **; Note: IFU states “For Intravenous Infusion Only” | 0.5% METRONIDAZOL IV solution for infusion
Language of the Labels | English | Turkish*
Indications | To reduce the development of drug-resistant bacteria and maintain the effectiveness of Metronidazole Injection USP and other antibacterial drugs, Metronidazole Injection USP should be used only to treat or prevent infections that are proven or strongly suspected to be caused by susceptible bacteria. | • Medical and surgical infections caused by anaerobic bacteria sensitive to metronidazole in the treatment of infections,; • For prophylactic purposes in surgical procedures with a risk of anaerobic infection development,; • It is indicated in severe intestinal and hepatic amebiasis.
Active Ingredients | Each 100 ml contains 500mg metronidazole | Each 100 ml contains 500mg metronidazole
Store Conditions | Store at room temperature 25C/77F | Store at below 30C
Container Type | PAB® Container | Polypropylene

*Upon receiving Submission Acceptance Turk Ilac ve Serum Sanayi will have bag labels written in both Turkish and English.

** Injections are quick procedures, typically completed in a few seconds to minutes, and involve delivering a single dose of medication directly into the muscle, skin, or vein. Infusions, on the other hand, take longer and involve a continuous flow of medication directly into the bloodstream. However, 100ml bags of Metronidazole can be used for both infusions and injections as their intended use is the same. Because of their small volume, they can be used together for infusions and injections, and in some cases, they are even administered concurrently or sequentially through the same IV line, depending on the medical need and drug compatibility.

Table 2: Label Images of FDA-approved and Turkfleks %0.9 Sodium Chloride Injection